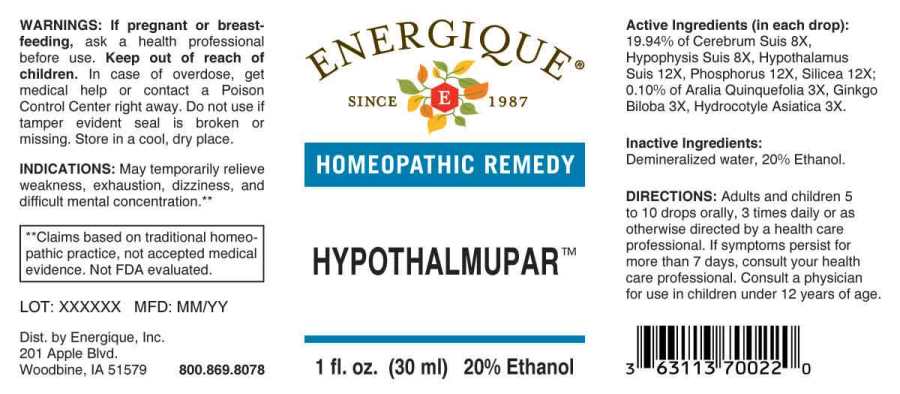 DRUG LABEL: Hypothalmupar
NDC: 44911-0473 | Form: LIQUID
Manufacturer: Energique, Inc.
Category: homeopathic | Type: HUMAN OTC DRUG LABEL
Date: 20241028

ACTIVE INGREDIENTS: AMERICAN GINSENG 3 [hp_X]/1 mL; GINKGO 3 [hp_X]/1 mL; CENTELLA ASIATICA WHOLE 3 [hp_X]/1 mL; SUS SCROFA CEREBRUM 8 [hp_X]/1 mL; SUS SCROFA PITUITARY GLAND 8 [hp_X]/1 mL; SUS SCROFA HYPOTHALAMUS 12 [hp_X]/1 mL; PHOSPHORUS 12 [hp_X]/1 mL; SILICON DIOXIDE 12 [hp_X]/1 mL
INACTIVE INGREDIENTS: WATER; ALCOHOL

DRUG FACTS:

ACTIVE INGREDIENTS:

(in each drop): 19.94% of Cerebrum Suis 8X, Hypophysis Suis 8X, Hypothalamus Suis 12X, Phosphorus 12X, Silicea 12X; 0.10% of Aralia Quinquefolia 3X, Ginkgo Biloba 3X, Hydrocotyle Asiatica 3X.

INDICATIONS:

May temporarily relieve weakness, exhaustion, dizziness, and difficult mental concentration.**

**Claims based on traditional homeopathic practice, not accepted medical evidence. Not FDA evaluated.

WARNINGS:

If pregnant or breast-feeding, ask a health professional before use.

Keep out of reach of children. In case of overdose, get medical help or contact a Poison Control Center right away.

Do not use if tamper evident seal is broken or missing. Store in a cool, dry place.

Keep out of reach of children. In case of overdose, get medical help or contact a Poison Control Center right away.

DIRECTIONS:

Adults and children 5 to 10 drops orally, 3 times daily or as otherwise directed by a health care professional. If symptoms persist for more than 7 days, consult your health care professional. Consult a physician for use in children under 12 years of age.

INDICATIONS:

May temporarily relieve weakness, exhaustion, dizziness, and difficult mental concentration.**

**Claims based on traditional homeopathic practice, not accepted medical evidence. Not FDA evaluated.

INACTIVE INGREDIENTS:

Demineralized water, 20% Ethanol.

QUESTIONS:

Dist. by Energique, Inc.

201 Apple Blvd

Woodbine, IA 51579 800.869.8078

PACKAGE LABEL DISPLAY:

ENERGIQUE

SINCE 1987

HOMEOPATHIC REMEDY

HYPOTHALMUPAR

1 fl. oz. (30 ml)